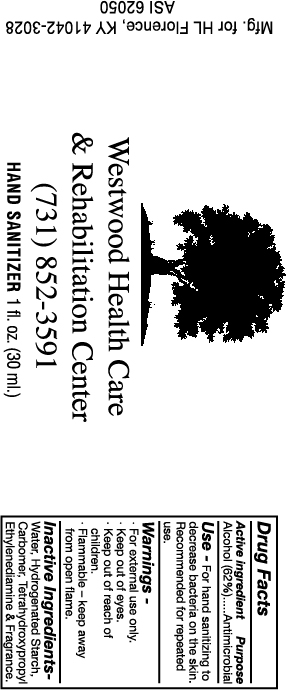 DRUG LABEL: Hand Sanitizer
NDC: 19392-210 | Form: LIQUID
Manufacturer: Humphreyline
Category: otc | Type: HUMAN OTC DRUG LABEL
Date: 20120719

ACTIVE INGREDIENTS: ALCOHOL 620 mL/1000 mL
INACTIVE INGREDIENTS: WATER; CARBOMER HOMOPOLYMER TYPE C (ALLYL PENTAERYTHRITOL CROSSLINKED); EDETOL

Drug Facts

ACTIVE INGREDIENT

Alcohol (62%)

PURPOSE

Antimicrobial

Keep out of reach of children

INDICATIONS AND USAGE

For hand sanitizing to decrease bacteria on the skin. Recommended for repeated use.

WARNINGS

For external use only

Keep out of eyes

Keep out of reach of children

Flammable-keep away from open flame

DOSAGE AND ADMINISTRATION

Recommended for repeated use

INACTIVE INGREDIENT

Water, Hydrogenated starch, Carbomer, Tetrahydroxypropyl Ethylenediamine, Fragrance